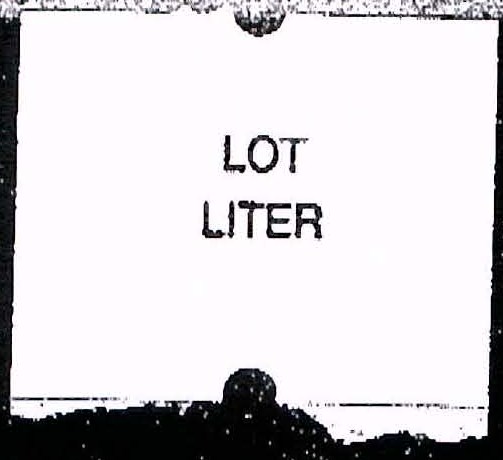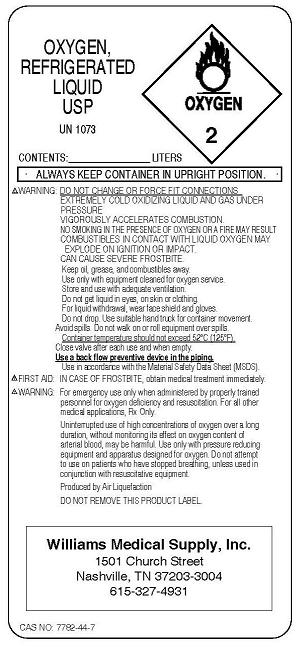 DRUG LABEL: Oxygen
NDC: 63565-0001 | Form: GAS
Manufacturer: Williams Medical Supply, Inc.
Category: prescription | Type: HUMAN PRESCRIPTION DRUG LABEL
Date: 20091204

ACTIVE INGREDIENTS: Oxygen 99 L/100 L

Oxygen